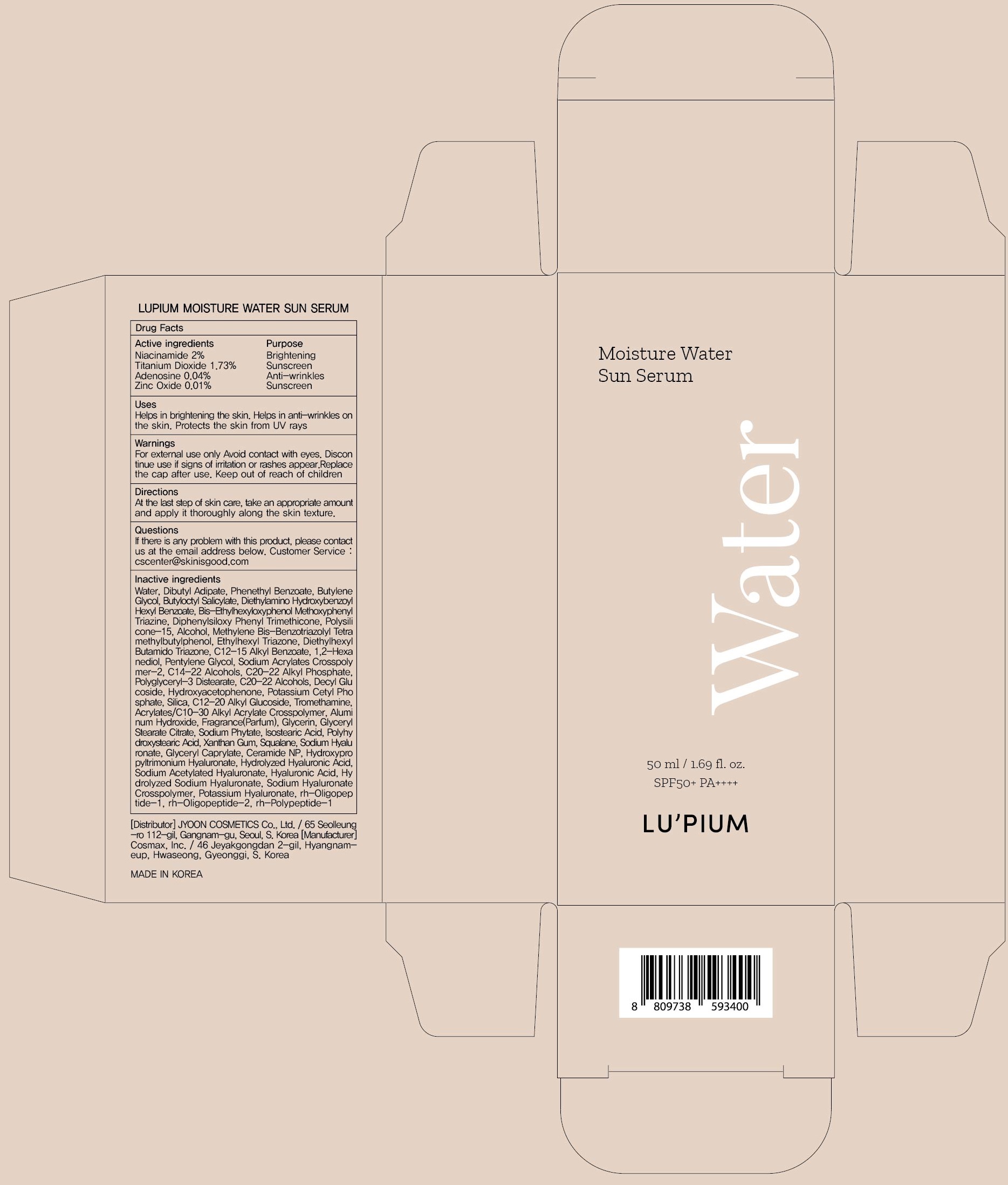 DRUG LABEL: LUPIUM MOISTURE WATER SUN SERUM
NDC: 82284-010 | Form: LIQUID
Manufacturer: JYOONCOSMETICS Co, Ltd
Category: otc | Type: HUMAN OTC DRUG LABEL
Date: 20211012

ACTIVE INGREDIENTS: Niacinamide 1.00 g/50 mL; Titanium Dioxide 0.86 g/50 mL; Adenosine 0.02 g/50 mL; Zinc Oxide 0.005 g/50 mL
INACTIVE INGREDIENTS: Water; Dibutyl Adipate

ACTIVE INGREDIENTS

Niacinamide 2%
Titanium Dioxide 1.73%
Adenosine 0.04%
Zinc Oxide 0.01%

INACTIVE INGREDIENTS

Water, Dibutyl Adipate, Phenethyl Benzoate, Butylene Glycol, Butyloctyl Salicylate, Diethylamino Hydroxybenzoyl Hexyl Benzoate, Bis-Ethylhexyloxyphenol Methoxyphenyl Triazine, Diphenylsiloxy Phenyl Trimethicone, Polysilicone-15, Alcohol, Methylene Bis-Benzotriazolyl Tetramethylbutylphenol, Ethylhexyl Triazone, Diethylhexyl Butamido Triazone, C12-15 Alkyl Benzoate, 1,2-Hexanediol, Pentylene Glycol, Sodium Acrylates Crosspolymer-2, C14-22 Alcohols, C20-22 Alkyl Phosphate, Polyglyceryl-3 Distearate, C20-22 Alcohols, Decyl Glucoside, Hydroxyacetophenone, Potassium Cetyl Phosphate, Silica, C12-20 Alkyl Glucoside, Tromethamine, Acrylates/C10-30 Alkyl Acrylate Crosspolymer, Aluminum Hydroxide, Fragrance(Parfum), Glycerin, Glyceryl Stearate Citrate, Sodium Phytate, Isostearic Acid, Polyhydroxystearic Acid, Xanthan Gum, Squalane, Sodium Hyaluronate, Glyceryl Caprylate, Ceramide NP, Hydroxypropyltrimonium Hyaluronate, Hydrolyzed Hyaluronic Acid, Sodium Acetylated Hyaluronate, Hyaluronic Acid, Hydrolyzed Sodium Hyaluronate, Sodium Hyaluronate Crosspolymer, Potassium Hyaluronate, rh-Oligopeptide-1, rh-Oligopeptide-2, rh-Polypeptide-1

PURPOSE

Brightening, Sunscreen, Anti-wrinkles

WARNINGS

For external use only
Avoid contact with eyes.
Discontinue use if signs of irritation or rashes appear.
Replace the cap after use.
Keep out of reach of children

KEEP OUT OF REACH OF CHILDREN

Uses

Helps in brightening the skin.
Helps in anti-wrinkles on the skin.
Protects the skin from UV rays

Directions

At the last step of skin care, take an appropriate amount and apply it thoroughly along the skin texture.

QUESTIONS

If there is any problem with this product, please contact us at the email address below. Customer Service : cscenter@skinisgood.com